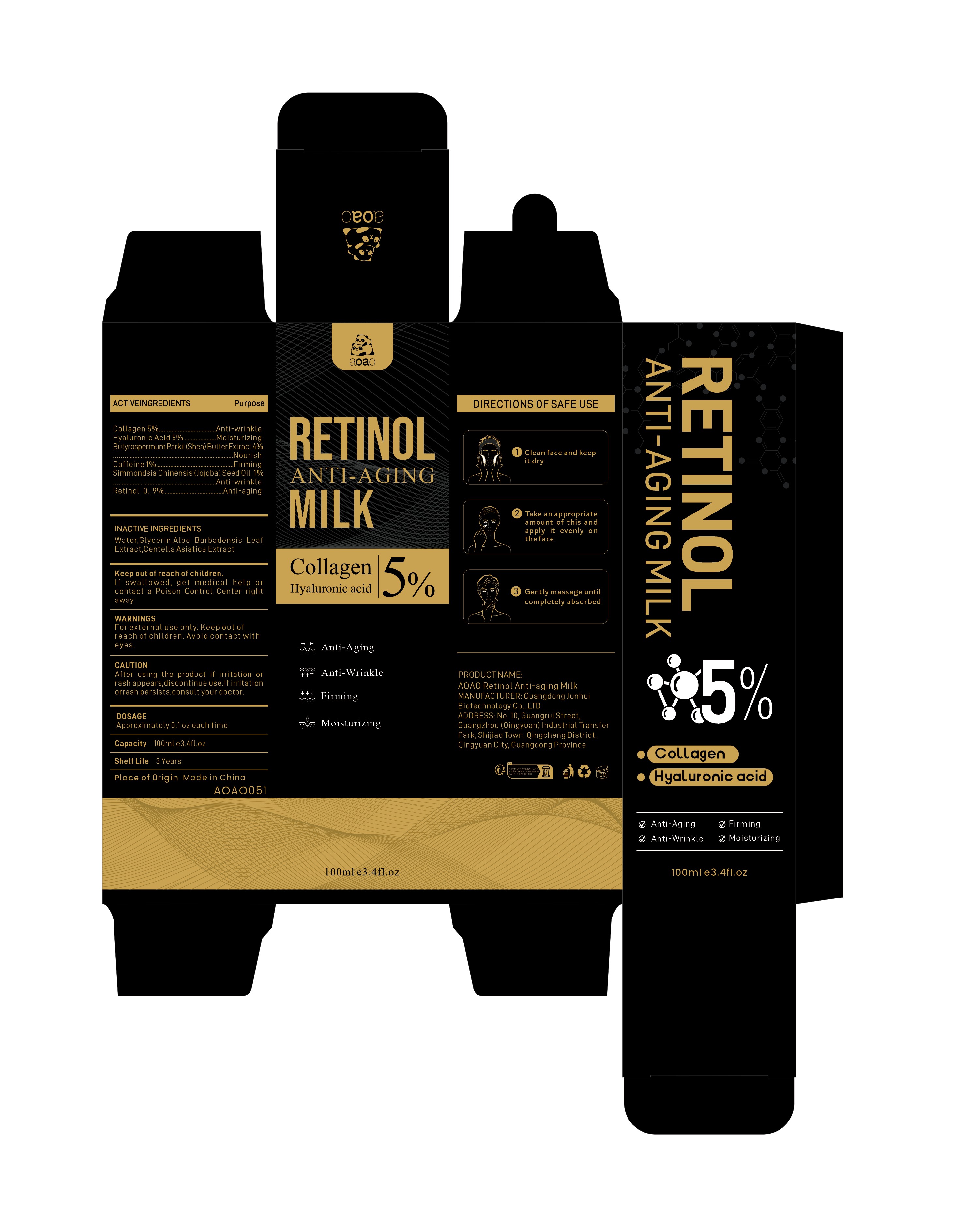 DRUG LABEL: AOAO Retinol Anti-aging Milk
NDC: 84509-047 | Form: EMULSION
Manufacturer: Guangdong Junhui Biotechnology Co., LTD
Category: otc | Type: HUMAN OTC DRUG LABEL
Date: 20241107

ACTIVE INGREDIENTS: BUTYROSPERMUM PARKII (SHEA) BUTTER EXTRACT 4000 mg/100 mL; HYALURONIC ACID 5000 mg/100 mL; RETINOL 900 mg/100 mL; COLLAGEN, SOLUBLE, FISH SKIN 5000 mg/100 mL; CAFFEINE 1000 mg/100 mL; SIMMONDSIA CHINENSIS (JOJOBA) SEED OIL 1000 mg/100 mL
INACTIVE INGREDIENTS: WATER; CENTELLA ASIATICA TRITERPENOIDS; ALOE BARBADENSIS LEAF EXTRACT; GLYCERIN

Active Ingredients

Collagen 5%
Butyrospermum Parkii (Shea) Butter Extract 4%
Hyaluronic Acid 5%
Caffeine 1%
Simmondsia Chinensis (Jojoba) Seed Oil 1%
Retinol 0.9%

Purpose

Anti-wrinkle
Nourish
Moisturizing
Firming
Anti-aging

Uses

1、After cleansing use the Rice andCeramide Moisturizing Toner toprep the skin
2、Apply the Rice and CeramideMoisturizing Emulsion tomoisturize the skin
3、Use the Rice & CeramideMoisturizing Cream to plump andsoften the skin

Warnings

For external use only. Keep out ofreach of children.Avoid contact with eyes

Keep out of reach of children

If swallowed, get medical help or contact a Poison Control Center right away

CAUTION

After using the product if irritation or rash appears,discontinue use.If irritation or rash persists.consult your doctor.

Inactive Ingredients

Water,Glycerin，Aloe Barbadensis Leaf Extract，Centella Asiatica Extract，

DOSAGE

Approximately 0.1fl.oz each time

Product Name

AOAO Retinol Anti-aging Milk

Manufacturer

Guangdong Junhui Biotechnology Co., LTD

ADDRESS

No. 10, Guangrui Street, Guangzhou (Qingyuan) Industrial Transfer Park, Shijiao Town, Qingcheng District, Qingyuan City, Guangdong Province

Capacity

100ml e3.4fl.oz

Shelf Life

3 Years

Place of Origin

Made in China